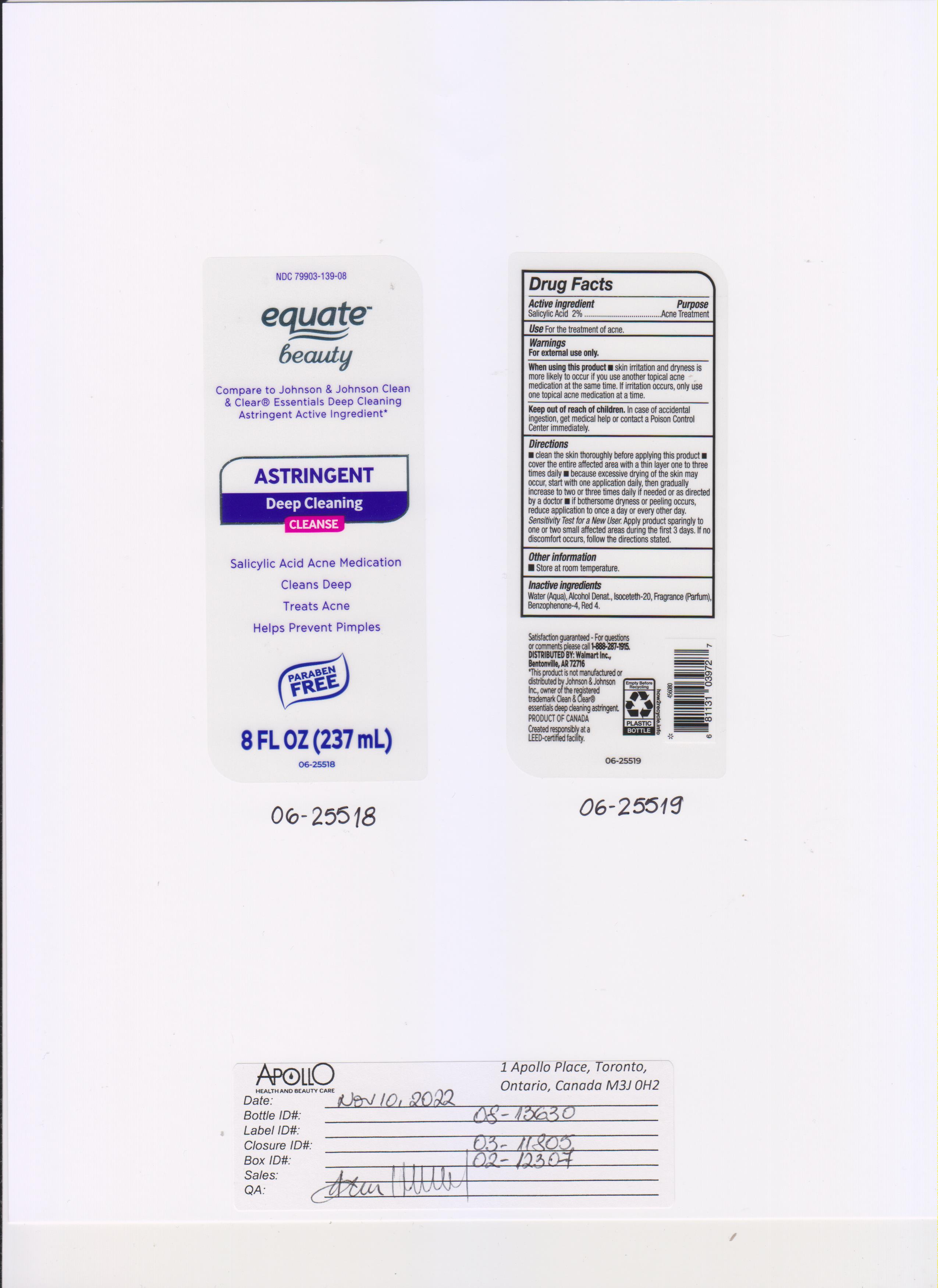 DRUG LABEL: Equate Beauty
NDC: 79903-139 | Form: SOAP
Manufacturer: WALMART INC
Category: otc | Type: HUMAN OTC DRUG LABEL
Date: 20250206

ACTIVE INGREDIENTS: SALICYLIC ACID 2000 mg/100 mL
INACTIVE INGREDIENTS: BENZOPHENONE-4; ISOCETETH-20; ALCOHOL; FRAGRANCE CLEAN ORC0600327; FD&C RED NO. 4; WATER

NDC- 79903-139, Astringent Deep Cleaning

ACTIVE INGREDIENT

Salicylic Acid

PURPOSE

Acne treatment

INDICATIONS AND USAGE

Use: For the treatment of acne

WARNINGS

- For external use only.
- Flammable
- Keep away form source of heat or fire

Ask doctor or pharmacist before use if you are using other topical acne medications at the same time or immediately following use of this product. This may increase dryness or irritation of the skin. If this occurs, only one medication should be used unless otherwise
directed by a doctor.

When using this product avoid contact with eyes. If contact occurs, rinse eyes thoroughly with water for 15 minutes.

Stop use and ask a doctor if irritation, dryness or redness develops and lasts. Ask doctor before use if pregnant/breastfeeding.

Keep out of reach of children. In case of accidental ingestion, get medical help or contact a Poison Control Center immediately.

Directions

New Users: Apply to small area before use to test for sensitivity, If no discomfort occurs, apply to affected area and rinse off. Start with one application and gradually increase to 2-3 times daily if needed or as directed by physician.

Other Information

Store at room temperature.

Inactive Ingredients

Water, Alcohol Denat, Isoceteth-20, Fragrance (Parfum), Benzophenone-4, Red 4